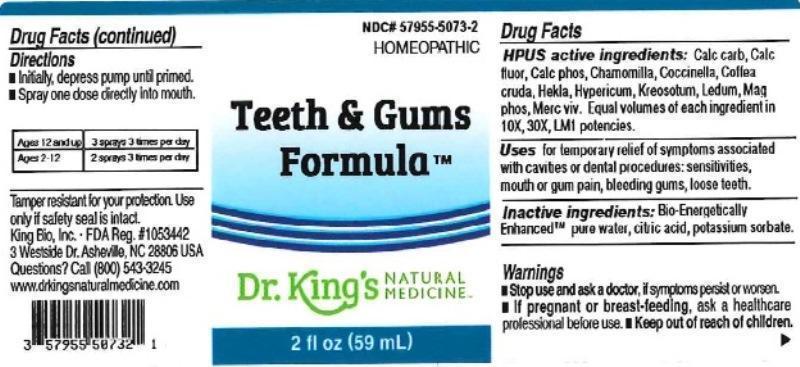 DRUG LABEL: Teeth and Gums Formula
NDC: 57955-5073 | Form: LIQUID
Manufacturer: King Bio Inc.
Category: homeopathic | Type: HUMAN OTC DRUG LABEL
Date: 20160624

ACTIVE INGREDIENTS: OYSTER SHELL CALCIUM CARBONATE, CRUDE 10 [hp_X]/59 mL; CALCIUM FLUORIDE 10 [hp_X]/59 mL; TRIBASIC CALCIUM PHOSPHATE 10 [hp_X]/59 mL; MATRICARIA RECUTITA 10 [hp_X]/59 mL; COCCINELLA SEPTEMPUNCTATA 10 [hp_X]/59 mL; ARABICA COFFEE BEAN 10 [hp_X]/59 mL; HEKLA LAVA 10 [hp_X]/59 mL; HYPERICUM PERFORATUM 10 [hp_X]/59 mL; WOOD CREOSOTE 10 [hp_X]/59 mL; LEDUM PALUSTRE TWIG 10 [hp_X]/59 mL; MAGNESIUM PHOSPHATE, DIBASIC TRIHYDRATE 10 [hp_X]/59 mL; MERCURY 10 [hp_X]/59 mL
INACTIVE INGREDIENTS: ANHYDROUS CITRIC ACID; POTASSIUM SORBATE; WATER

Teeth and Gums Formula™

ACTIVE INGREDIENT

Drug Facts__________________________________________________________________________________________________________

HPUS active ingredients: Calcarea carbonica, Calcarea fluorica, Calcarea phosphorica, Chamomilla, Coccinella septempunctata, Coffea cruda, Hekla lava, Hypericum perforatum, Kreosotum, Ledum palustre, Magnesia phosphorica, Mercurius vivus. Equal volumes of each ingredient in 10X, 30X, LM1 potencies.

INDICATIONS AND USAGE

Uses for temporary relief of symptoms associated with cavities or dental procedures: sensitivities, mouth or gum pain, bleeding gums, loose teeth.

Inactive Ingredients:

Bio-Energetically Enhanced™ pure water, citric acid and potassium sorbate.

Warnings

- Stop use and ask your doctor if symptoms persist or worsen.
- If pregnant or breast-feeding, ask a healthcare professional before use.

- Keep out of reach of children.

Directions

- Initially, depress pump until primed.
- Spray one dose directly into mouth.
- Ages 12 and up: 3 sprays 3 times per day.
- Ages 2-12: 2 sprays 3 times per day.

OTHER SAFETY INFORMATION

Tamper resistant for your protection. Use only if safety seal is intact.

PURPOSE

Uses for temporary relief of symptoms associated with cavities or dental procedures:

- sensitivities
- mouth or gum pain
- bleeding gums
- loose teeth